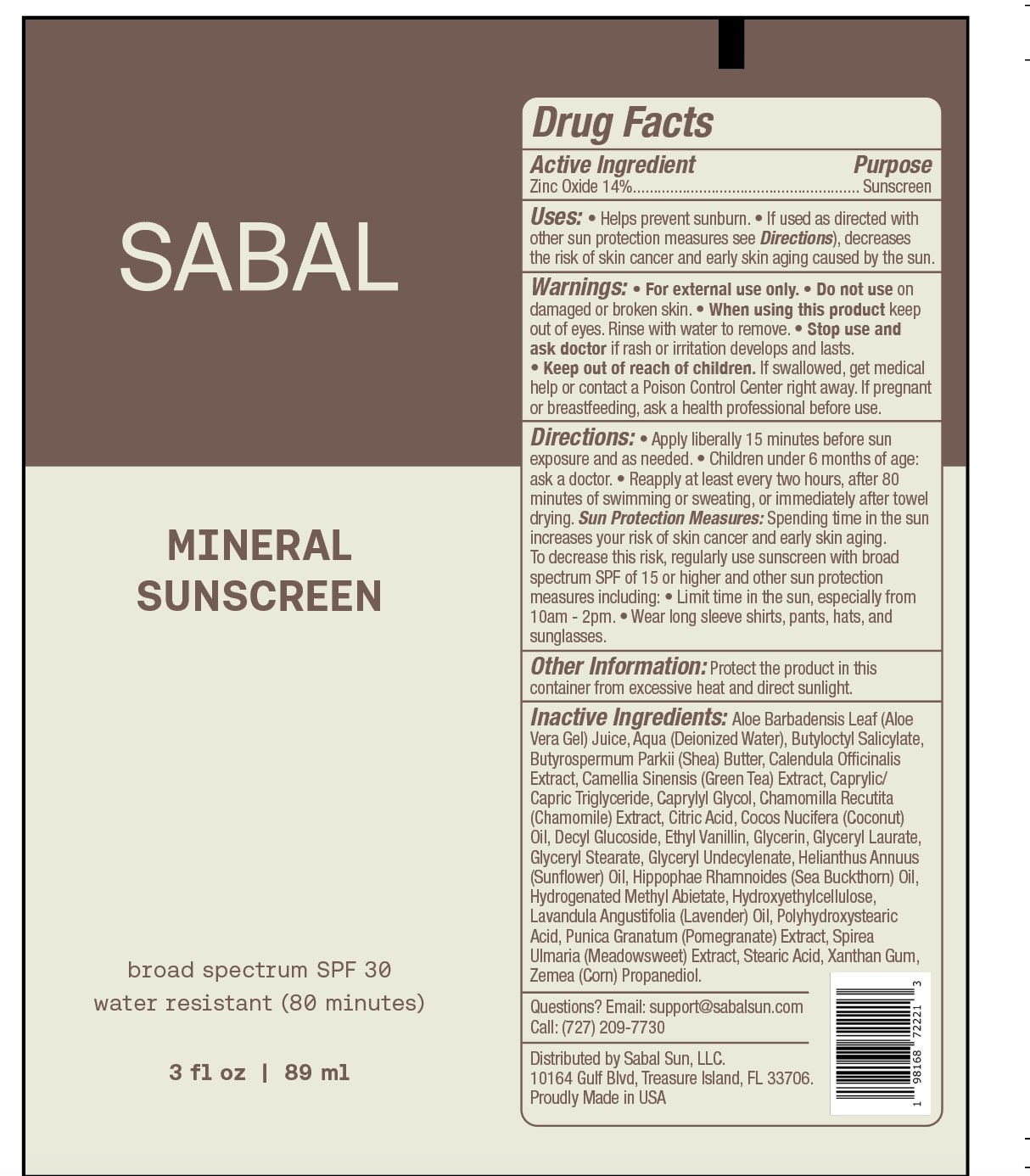 DRUG LABEL: SABAL Mineral Sunscreen Broad Sprectrum SPF 30
NDC: 84446-505 | Form: LOTION
Manufacturer: SABAL SUN LLC
Category: otc | Type: HUMAN OTC DRUG LABEL
Date: 20260119

ACTIVE INGREDIENTS: ZINC OXIDE 140 mg/1 mL
INACTIVE INGREDIENTS: ALOE VERA LEAF; WATER; BUTYLOCTYL SALICYLATE; SHEA BUTTER; CALENDULA OFFICINALIS FLOWER; GREEN TEA LEAF; MEDIUM-CHAIN TRIGLYCERIDES; CAPRYLYL GLYCOL; CHAMOMILE; CITRIC ACID MONOHYDRATE; COCONUT OIL; DECYL GLUCOSIDE; ETHYL VANILLIN; GLYCERIN; GLYCERYL LAURATE; GLYCERYL MONOSTEARATE; HELIANTHUS ANNUUS FLOWERING TOP; HYDROGENATED METHYL ABIETATE; HYDROXYETHYL CELLULOSE, UNSPECIFIED; LAVENDER OIL; PUNICA GRANATUM ROOT BARK; STEARIC ACID; XANTHAN GUM; CORN

SABAL Mineral Sunscreen Broad Sprectrum SPF-30

Active Ingredient

Zinc Oxide 14%

Purpose

Sunscreen

Uses:

- Helps prevent sunburn.
- If used as directed with other sun protection measures see Directions), decreases the risk of skin cancer and early skin aging caused by the sun.

Warnings:

- For external use only.

Do not use

- on damaged or broken skin.

When using this product

- keep out of eyes. Rinse with water to remove.

Stop use and ask doctor

- if rash or irritation develops and lasts.

Keep out of reach of children.

- If swallowed, get medical help or contact a Poison Control Center right away.

If pregnant or breastfeeding,

ask a health professional before use.

Directions:

- Apply liberally 15 minutes before sun exposure and as needed.
- Children under 6 months of age: ask a doctor.
- Reapply at least every two hours, after 80 minutes of swimming or sweating, or immediately after towel drying.

Sun Protection Measures: Spending time in the sun increases your risk of skin cancer and early skin aging. To decrease this risk, regularly use sunscreen with broad spectrum SPF of 15 or higher and other sun protection measures including:

- Limit time in the sun, especially from 10am - 2pm.
- Wear long sleeve shirts, pants, hats, and sunglasses.

Other Information:

Protect the product in this container from excessive heat and direct sunlight.

Inactive Ingredients:

Aloe Barbadensis Leaf (Aloe Vera Gel) Juice, Aqua (Deionized Water), Butyloctyl Salicylate, Butyrospermum Parkii (Shea) Butter, Calendula Officinalis Extract, Camellia Sinensis (Green Tea) Extract, Caprylic/Capric Triglyceride, Caprylyl Glycol, Chamomilla Recutita (Chamomile) Extract, Citric Acid, Cocos Nucifera (Coconut) Oil, Decyl Glucoside, Ethyl Vanillin, Glycerin, Glyceryl Laurate, Glyceryl Stearate, Glyceryl Undecylenate, Helianthus Annuus (Sunflower) Oil, Hippophae Rhamnoides (Sea Buckthorn) Oil, Hydrogenated Methyl Abietate, Hydroxyethylcellulose, Lavandula Angustifolia (Lavender) Oil, Polyhydroxystearic Acid, Punica Granatum (Pomegranate) Extract, Spirea Ulmaria (Meadowsweet) Extract, Stearic Acid, Xanthan Gum, Zemea (Corn) Propanediol.

Questions?

Email: support@sabalsun.com

Call:(727)-209-7730